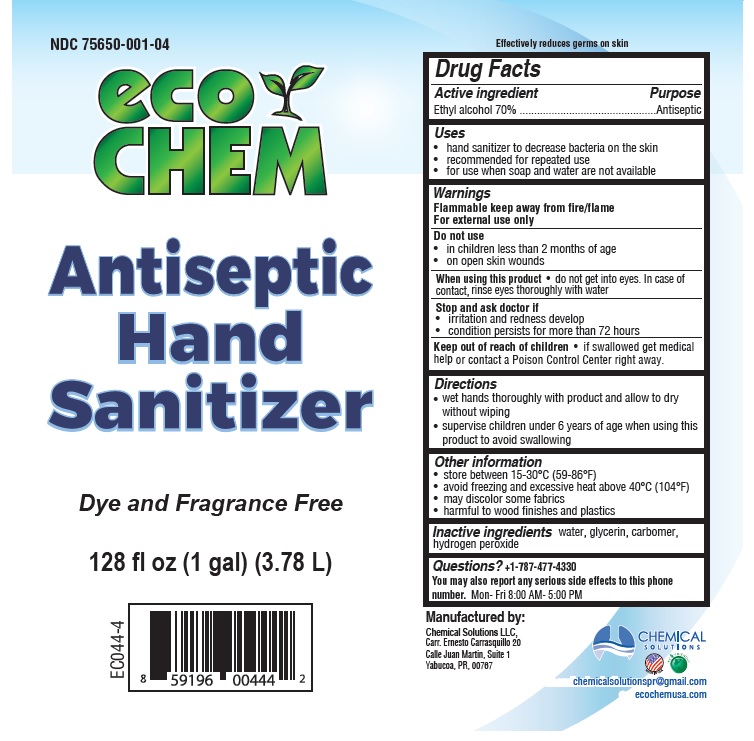 DRUG LABEL: Eco Chem Antiseptic Hand Sanitizer
NDC: 75650-001 | Form: LIQUID
Manufacturer: Chemical Solutions, Llc
Category: otc | Type: HUMAN OTC DRUG LABEL
Date: 20200417

ACTIVE INGREDIENTS: ALCOHOL 0.7 L/1 L
INACTIVE INGREDIENTS: WATER; GLYCERIN; CARBOMER HOMOPOLYMER, UNSPECIFIED TYPE; HYDROGEN PEROXIDE

eco CHEM Antiseptic Hand Sanitizer

Active ingredient

Ethyl alcohol 70%

Purpose

Antiseptic

Uses

- hand sanitizer to decrease bacteria on the skin
- recommended for repeated use
- for use when soap and water are not available

Warnings

Flammable. Keep away from fire/flame

For external use only

Do not use

- in children less than 2 months of age
- on open skin wounds

When using this product • do not get into eyes. In case of contact, rinse eyes thoroughly with water.

Stop and ask a doctor if

- irritation and redness develops
- condition persists for more than 72 hours.

Keep out of reach of children. if swallowed, get medical help or contact a Poison Control Center right away.

Directions

- wet hands thoroughly with product and allow to dry without wiping
- supervise children under 6 years of age when using this product to avoid swallowing

Other Information

- store between 15-30°C (59-86°F)
- avoid freezing and excessive heat above 40°C (104°F)
- may discolor some fabrics
- harmful to wood finishes and plastics

Inactive ingredients

water, glycerin, carbomer, hydrogen peroxide

Questions?

+1-787-477-4330

You may also report serious side effects to this phone number.

Mon- Fri 8:00 AM - 5.00 PM

Dye and Fragrance Free

Effectively reduces germs on skin.

Manufactured by:

Chemical solutions LLC

Carr. Ernesto Carrasquillo 20

Calle Juan Martin, Suite 1

Yabucoa, PR, 00767

MADE IN USA

chemicalsolutionspr@gmail.com

ecochemusa.com